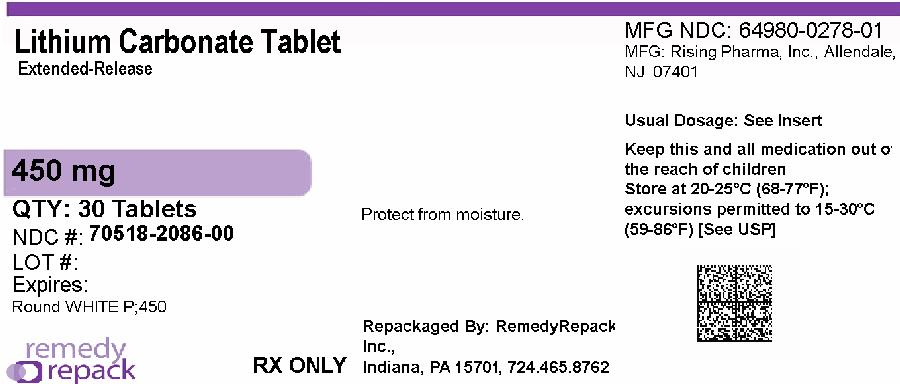 DRUG LABEL: Lithium Carbonate
NDC: 70518-2086 | Form: TABLET, EXTENDED RELEASE
Manufacturer: REMEDYREPACK INC.
Category: prescription | Type: HUMAN PRESCRIPTION DRUG LABEL
Date: 20260130

ACTIVE INGREDIENTS: LITHIUM CARBONATE 450 mg/1 1
INACTIVE INGREDIENTS: SODIUM ALGINATE; SODIUM STARCH GLYCOLATE TYPE A POTATO; FERRIC OXIDE YELLOW; MAGNESIUM STEARATE; POVIDONE K30

LITHIUM CARBONATE EXTENDED-RELEASE TABLETS USP, 450 mg
Rx Only

WARNING

Lithium toxicity is closely related to serum lithium levels, and can occur at doses close to therapeutic levels. Facilities for prompt and accurate serum lithium determinations should be available before initiating therapy
(see DOSAGE AND ADMINISTRATION).

DESCRIPTION

Lithium Carbonate Extended-Release Tablets contains lithium carbonate, a white, light alkaline powder with molecular formula Li2CO3and molecular weight 73.89. Lithium is an element of the alkali-metal group with atomic number 3, atomic weight 6.94 and an emission line at 671 nm on the flame photometer.

Lithium Carbonate Extended-Release Tablets:Each white to off white round tablets scored on one side and engraved with P;450 on the other side, contains lithium carbonate, 450 mg.
Inactive ingredients consist of sodium alginate, sodium starch glycolate, povidone, ferric oxide yellow, and magnesium stearate.

Lithium Carbonate Extended-Release Tablets 450 mg are designed to release a portion of the dose initially and the remainder gradually; the release pattern of the controlled release tablets reduces the variability in lithium blood levels seen with the immediate release dosage forms.

Meets USP Dissolution Test 2

CLINICAL PHARMACOLOGY

Preclinical studies have shown that lithium alters sodium transport in nerve and muscle cells and effects a shift toward intraneuronal metabolism of catecholamines, but the specific biochemical mechanism of lithium action in mania is unknown.

INDICATIONS AND USAGE

Lithium Carbonate Extended-Release Tablets is indicated in the treatment of manic episodes of manic-depressive illness. Maintenance therapy prevents or diminishes the intensity of subsequent episodes in those manic-depressive patients with a history of mania.

Typical symptoms of mania include pressure of speech, motor hyperactivity, reduced need for sleep, flight of ideas, grandiosity, elation, poor judgment, aggressiveness and possibly hostility. When given to a patient experiencing a manic episode, Lithium Carbonate Extended-Release Tablets may produce a normalization of symptomatology within 1 to 3 weeks.

WARNINGS

Lithium Toxicity

The toxic concentrations for lithium (≥1.5 mEq/L) are close to the therapeutic range (0.8 to 1.2mEq/L). Some patients abnormally sensitive to lithium may exhibit toxic signs at serum concentrations that are considered within the therapeutic range [see Boxed Warning, Dosage and Administration]. Lithium may take up to 24 hours to distribute into brain tissue, so occurrence of acute toxicity symptoms may be delayed.

Neurological signs of lithium toxicity range from mild neurological adverse reactions such as fine tremor, lightheadedness, lack of coordination, and weakness; to moderate manifestations like giddiness, apathy, drowsiness, hyperreflexia, muscle twitching, ataxia, blurred vision, tinnitus, and slurred speech; and severe manifestations such as clonus, confusion, seizure, coma, and death. In rare cases, neurological sequelae may persist despite discontinuing lithium treatment and may be associated with cerebellar atrophy. Cardiac manifestations involve electrocardiographic changes, such as prolonged QT interval, ST and T-wave changes and myocarditis. Renal manifestations include urine concentrating defect, nephrogenic diabetes insipidus, and renal failure. Respiratory manifestations include dyspnea, aspiration pneumonia, and respiratory failure. Gastrointestinal manifestations include nausea, vomiting, diarrhea, and bloating. No specific antidote for lithium poisoning is known [see Overdosage].

The risk of lithium toxicity is increased by:
• Recent onset of concurrent febrile illness
• Concomitant administration of drugs which increase lithium serum concentrations by pharmacokinetic interactions or drugs affecting kidney function [see Precautions-Drug Interactions]
• Acute ingestion
• Impaired renal function
• Volume depletion or dehydration
• Significant cardiovascular disease
• Changes in electrolyte concentrations (especially sodium and potassium)

Monitor for signs and symptoms of lithium toxicity. If symptoms occur, decrease dosage or discontinue lithium treatment.

Unmasking of Brugada Syndrome

There have been postmarketing reports of a possible association between treatment with lithium and the unmasking of Brugada Syndrome. Brugada Syndrome is a disorder characterized by abnormal electrocardiographic (ECG) findings and a risk of sudden death. Lithium should generally be avoided in patients with Brugada Syndrome or those suspected of having Brugada Syndrome. Consultation with a cardiologist is recommended if: (1) treatment with lithium is under consideration for patients suspected of having Brugada Syndrome or patients who have risk factors for Brugada Syndrome, e.g., unexplained syncope, a family history of Brugada Syndrome, or a family history of sudden unexplained death before the age of 45 years, (2) patients who develop unexplained syncope or palpitations after starting lithium therapy.

Pseudotumor Cerebri

Cases of pseudotumor cerebri (increased intracranial pressure and papilledema) have been reported with lithium use. If undetected, this condition may result in enlargement of the blind spot, constriction of visual fields, and eventual blindness due to optic atrophy. Lithium should be discontinued, if clinically possible, if this syndrome occurs.

Renal Effects
Chronic lithium therapy may be associated with diminution of renal concentrating ability, occasionally presenting as nephrogenic diabetes insipidus, with polyuria and polydipsia. Such patients should be carefully managed to avoid dehydration with resulting lithium retention and toxicity. This condition is usually reversible when lithium is discontinued.

Post marketing cases consistent with nephrotic syndrome have been reported with the use of lithium. Biopsy findings in patients with nephrotic syndrome include minimal change disease and focal segmental glomerulosclerosis. Discontinuation of lithium in patients with nephrotic syndrome has resulted in remission of nephrotic syndrome.

Morphologic changes with glomerular and interstitial fibrosis and nephron atrophy have been reported in patients on chronic lithium therapy. Morphologic changes have also been seen in manic-depressive patients never exposed to lithium. The relationship between renal functional and morphologic changes and their association with lithium therapy have not been established.

Kidney function should be assessed prior to and during lithium therapy. Routine urinalysis and other tests may be used to evaluate tubular function (e.g., urine specific gravity or osmolality following a period of water deprivation, or 24-hour urine volume) and glomerular function (e.g., serum creatinine, creatinine clearance or proteinuria). During lithium therapy, progressive or sudden changes in renal function, even within the normal range, indicate the need for reevaluation of treatment.

Encephalopathic Syndrome
An encephalopathic syndrome (characterized by weakness, lethargy, fever, tremulousness and confusion, extrapyramidal symptoms, leukocytosis, elevated serum enzymes, BUN and FBS) has occurred in a few patients treated with lithium plus a neuroleptic. In some instances, the syndrome was followed by irreversible brain damage. Because of a possible causal relationship between these events and the concomitant administration of lithium and neuroleptics, patients receiving such combined therapy should be monitored closely for early evidence of neurologic toxicity and treatment discontinued promptly if such signs appear. This encephalopathic syndrome may be similar to or the same as neuroleptic malignant syndrome (NMS).

Serotonin Syndrome

Lithium can precipitate serotonin syndrome, a potentially life-threatening condition. The risk is increased with concomitant use of other serotonergic drugs (including selective serotonin reuptake inhibitors, serotonin and norepinephrine reuptake inhibitors, triptans, tricyclic antidepressants, fentanyl, tramadol, tryptophan, buspirone, and St. John’s Wort) and with drugs that impair metabolism of serotonin, i.e., MAOIs (see PRECAUTIONS).

Serotonin syndrome signs and symptoms may include mental status changes (e.g., agitation, hallucinations, delirium, and coma), autonomic instability (e.g., tachycardia, labile blood pressure, dizziness, diaphoresis, flushing, hyperthermia), neuromuscular symptoms (e.g., tremor, rigidity, myoclonus, hyperreflexia, incoordination), seizures, and gastrointestinal symptoms (e.g., nausea, vomiting, diarrhea).

Monitor all patients taking lithium for the emergence of serotonin syndrome. Discontinue treatment with lithium and any concomitant serotonergic agents immediately if the above symptoms occur, and initiate supportive symptomatic treatment. If concomitant use of lithium with other serotonergic drugs is clinically warranted, inform patients of the increased risk for serotonin syndrome and monitor for symptoms.

Concomitant Use with Neuromuscular Blocking Agents
Lithium may prolong the effects of neuromuscular blocking agents. Therefore, neuromuscular blocking agents should be given with caution to patients receiving lithium.
Usage in Pregnancy

Adverse effects on implantation in rats, embryo viability in mice and metabolism in vitroof rat testes and human spermatozoa have been attributed to lithium, as have teratogenicity in submammalian species and cleft palates in mice.

In humans, lithium carbonate may cause fetal harm when administered to a pregnant woman. Data from lithium birth registries suggest an increase in cardiac and other anomalies, especially Ebstein’s anomaly. If this drug is used in women of childbearing potential, or during pregnancy, or if a patient becomes pregnant while taking this drug, the patient should be apprised of the potential hazard to the fetus.
Usage in Nursing Mothers
Lithium is excreted in human milk. Nursing should not be undertaken during lithium therapy except in rare and unusual circumstances where, in the view of the physician, the potential benefits to the mother outweigh possible hazards to the infant or neonate. Signs and symptoms of lithium toxicity such as hypertonia, hypothermia, cyanosis, and ECG changes have been reported in some infants and neonates.
Usage in Pediatric Patients
Safety and effectiveness in pediatric patients under 12 years of age have not been determined; its use in these patients is not recommended.
There has been a report of a transient syndrome of acute dystonia and hyperreflexia occurring in a 15 kg child who ingested 300 mg of lithium carbonate.

PRECAUTIONS

General

The ability to tolerate lithium is greater during the acute manic phase and decreases when manic symptoms subside (see DOSAGE AND ADMINISTRATION).

The distribution space of lithium approximates that of total body water. Lithium is primarily excreted in urine with insignificant excretion in feces. Renal excretion of lithium is proportional to its plasma concentration. The half-life of elimination of lithium is approximately 24 hours. Lithium decreases sodium reabsorption by the renal tubules which could lead to sodium depletion. Therefore, it is essential for the patient to maintain a normal diet, including salt, and an adequate fluid intake (2,500 to 3,000 mL) at least during the initial stabilization period. Decreased tolerance to lithium has been reported to ensue from protracted sweating or diarrhea and, if such occur, supplemental fluid and salt should be administered under careful medical supervision and lithium intake reduced or suspended until the condition is resolved.

In addition to sweating and diarrhea, concomitant infection with elevated temperatures may also necessitate a temporary reduction or cessation of medication.

Previously existing underlying thyroid disorders do not necessarily constitute a contraindication to lithium treatment; where hypothyroidism preexists, careful monitoring of thyroid function during lithium stabilization and maintenance allows for correction of changing thyroid parameters, if any; where hypothyroidism occurs during lithium stabilization and maintenance, supplemental thyroid treatment may be used.

Information for Patients

Lithium carbonate may impair mental and/or physical abilities. Caution patients about activities requiring alertness (e.g., operating vehicles or machinery).

A condition known as Brugada Syndrome may pre-exist and be unmasked by lithium therapy. Brugada Syndrome is a heart disorder characterized by abnormal electrocardiographic (ECG) findings and risk of sudden death. Patients should be advised to seek immediate emergency assistance if they experience fainting, light-headedness, abnormal heart beats, or shortness of breath because they may have a potentially life-threatening heart disorder known as Brugada Syndrome.

Repackaged By / Distributed By: RemedyRepack Inc.

625 Kolter Drive, Indiana, PA 15701

(724) 465-8762

Drug Interactions

Caution should be used when lithium and diuretics are used concomitantly because diuretic-induced sodium loss may reduce the renal clearance of lithium and increase serum lithium levels with risk of lithium toxicity. Patients receiving such combined therapy should have serum lithium levels monitored closely and the lithium dosage adjusted if necessary.

Lithium levels should be closely monitored when patients initiate or discontinue NSAID use. In some cases, lithium toxicity has resulted from interactions between an NSAID and lithium. Indomethacin and piroxicam have been reported to increase significantly steady-state plasma lithium concentrations. There is also evidence that other nonsteroidal anti-inflammatory agents, including the selective cyclooxygenase-2 (COX-2) inhibitors, have the same effect. In a study conducted in healthy subjects, mean steady-state lithium plasma levels increased approximately 17% in subjects receiving lithium 450 mg b.i.d. with celecoxib 200 mg b.i.d. as compared to subjects receiving lithium alone.

Concomitant use of lithium with a Sodium-Glucose Cotransporter 2 (SGLT2) inhibitor may decrease serum lithium concentrations. Monitor serum lithium concentration more frequently during SGLT2 inhibitor initiation and dosage changes.

Concurrent use of metronidazole with lithium may provoke lithium toxicity due to reduced renal clearance. Patients receiving such combined therapy should be monitored closely.

There is evidence that angiotensin-converting enzyme inhibitors, such as enalapril and captopril, and angiotensin II receptor antagonists, such as losartan, may substantially increase steady-state plasma lithium levels, sometimes resulting in lithium toxicity. When such combinations are used, lithium dosage may need to be decreased, and plasma lithium levels should be measured more often.

Concurrent use of calcium channel blocking agents with lithium may increase the risk of neurotoxicity in the form of ataxia, tremors, nausea, vomiting, diarrhea, and/or tinnitus. Caution is recommended. Concomitant administration of lithium with serotonergic drugs can precipitate serotonin syndrome. Monitor patients for signs and symptoms of serotonin syndrome, particularly during lithium initiation. If serotonin syndrome occurs, consider discontinuation of lithium and/or concomitant serotonergic drugs. Examples of serotonergic drugs include selective serotonin reuptake inhibitors (SSRI), serotonin and norepinephrine reuptake inhibitors (SNRI), and monoamine oxidase inhibitors (MAOI).

The following drugs can lower serum lithium concentrations by increasing urinary lithium excretion: acetazolamide, urea, xanthine preparations, and alkalinizing agents such as sodium bicarbonate.

Concomitant administration of methyldopa, phenytoin, or carbamazepine with lithium may increase the risk of toxic effects of these drugs.

Concomitant extended use of iodide preparations, especially potassium iodide, with lithium may produce hypothyroidism.

Usage in Pregnancy
Teratogenic Effects: (See WARNINGS).
Usage in Nursing Mothers
Because of the potential for serious adverse reactions in nursing infants and neonates from lithium, a decision should be made whether to discontinue nursing or to discontinue the drug, taking into account the importance of the drug to the mother (see WARNINGS).

Pediatric Use

Safety and effectiveness in pediatric patients below the age of 12 have not been established (see WARNINGS).

Geriatric Use

Clinical studies of Lithium Carbonate Extended-Release Tablets did not include sufficient numbers of subjects aged 65 and over to determine whether they respond differently from younger subjects. Other reported clinical experience has not identified differences in responses between the elderly and younger patients. In general, dose selection for an elderly patient should be cautious, usually starting at the low end of the dosing range, reflecting the greater frequency of decreased hepatic, renal, or cardiac function, and of concomitant disease or other therapy.

This drug is known to be substantially excreted by the kidney, and the risk of toxic reactions to this drug may be greater in patients with impaired renal function. Because elderly patients are more likely to have decreased renal function, care should be taken in dose selection, and it may be useful to monitor renal function.

ADVERSE REACTIONS

The occurrence and severity of adverse reactions are generally directly related to serum lithium concentrations as well as to individual patient sensitivity to lithium, and generally occur more frequently and with greater severity at higher concentrations.

Adverse reactions may be encountered at serum lithium levels below 1.5 mEq/L. Mild to moderate adverse reactions may occur at levels from 1.5 to 2.5 mEq/L, and moderate to severe reactions may be seen at levels of 2.0 mEq/L and above.
Fine hand tremor, polyuria, and mild thirst may occur during initial therapy for the acute manic phase, and may persist throughout treatment. Transient and mild nausea and general discomfort may also appear during the first few days of lithium administration.
These side effects usually subside with continued treatment or a temporary reduction or cessation of dosage. If persistent, cessation of lithium therapy may be required. Diarrhea, vomiting, drowsiness, muscular weakness, and lack of coordination may be early signs of lithium intoxication, and can occur at lithium levels below 2.0 mEq/L. At higher levels, ataxia, giddiness, tinnitus, blurred vision, and a large output of dilute urine may be seen. Serum lithium levels above 3.0 mEq/L may produce a complex clinical picture, involving multiple organs and organ systems. Serum lithium levels should not be permitted to exceed 2.0 mEq/L during the acute treatment phase.
The following reactions have been reported and appear to be related to serum lithium levels, including levels within the therapeutic range:
Neuromuscular/Central Nervous System:Tremor, muscle hyperirritability (fasciculations, twitching, clonic movements of whole limbs), hypertonicity, ataxia, choreo-athetotic movements, hyperactive deep tendon reflex, extrapyramidal symptoms including acute dystonia, cogwheel rigidity, blackout spells, epileptiform seizures, slurred speech, dizziness, vertigo, downbeat nystagmus, incontinence of urine or feces, somnolence, psychomotor retardation, restlessness, confusion, stupor, coma, tongue movements, tics, tinnitus, hallucinations, poor memory, slowed intellectual functioning, startled response, worsening of organic brain syndromes, myasthenia gravis (rarely).
Cardiovascular:Cardiac arrhythmia, hypotension, peripheral circulatory collapse, bradycardia, sinus node dysfunction with severe bradycardia (which may result in syncope), Unmasking of Brugada Syndrome (See WARNINGSand PRECAUTIONS, Information for Patients).
Gastrointestinal:Anorexia, nausea, vomiting, diarrhea, gastritis, salivary gland swelling, abdominal pain, excessive salivation, flatulence, indigestion.
Genitourinary:Glycosuria, decreased creatinine clearance, albuminuria, oliguria, and symptoms of nephrogenic diabetes insipidus including polyuria, thirst and polydipsia.
Dermatologic:Drying and thinning of hair, alopecia, anesthesia of skin, chronic folliculitis, xerosis cutis, psoriasis onset or exacerbation, generalized pruritus with or without rash, cutaneous ulcers, angioedema, drug reaction with eosinophilia and systemic symptoms (DRESS).
Autonomic Nervous System: Blurred vision, dry mouth, impotence/sexual dysfunction.
Thyroid Abnormalities:Euthyroid goiter and/or hypothyroidism (including myxedema) accompanied by lower T3and T4. I^131uptake may be elevated. (See PRECAUTIONS.) Paradoxically, rare cases of hyperthyroidism have been reported.
EEG Changes:Diffuse slowing, widening of the frequency spectrum, potentiation and disorganization of background rhythm.
EKG Changes:Reversible flattening, isoelectricity or inversion of T-waves.
Miscellaneous:Fatigue, lethargy, transient scotomata, exophthalmos, dehydration, weight loss, leukocytosis, headache, transient hyperglycemia, hypercalcemia, hyperparathyroidism, excessive weight gain, edematous swelling of ankles or wrists, metallic taste, dysgeusia/taste distortion, salty taste, thirst, swollen lips, tightness in chest, swollen and/or painful joints, fever, polyarthralgia, dental caries.
Some reports of nephrogenic diabetes insipidus, hyperparathyroidism, and hypothyroidism which persist after lithium discontinuation have been received.
A few reports have been received of the development of painful discoloration of fingers and toes and coldness of the extremities within one day of the starting of treatment with lithium. The mechanism through which these symptoms (resembling Raynaud's syndrome) developed is not known. Recovery followed discontinuance.

OVERDOSAGE

The toxic levels for lithium (≥ 1.5 mEq/L) are close to the therapeutic levels (0.6 to 1.2 mEq/L). It is therefore important that patients and their families be cautioned to watch for early toxic symptoms and to discontinue the drug and inform the physician should they occur. Toxic symptoms are listed in detail under ADVERSE REACTIONS.

Treatment:No specific antidote for lithium poisoning is known. Early symptoms of lithium toxicity can usually be treated by reduction or cessation of dosage of the drug and resumption of the treatment at a lower dose after 24 to 48 hours. In severe cases of lithium poisoning, the first and foremost goal of treatment consists of elimination of this ion from the patient.
Treatment is essentially the same as that used in barbiturate poisoning: 1) gastric lavage, 2) correction of fluid and electrolyte imbalance, and 3) regulation of kidney function. Urea, mannitol and aminophylline all produce significant increases in lithium excretion. Hemodialysis is an effective and rapid means of removing the ion from the severely toxic patient.
Infection prophylaxis, regular chest X-rays and preservation of adequate respiration are essential.

DOSAGE AND ADMINISTRATION

Doses of controlled-release tablets are usually given b.i.d. (approximately 12-hour intervals). When initiating therapy with controlled-release lithium, dosage must be individualized according to serum levels and clinical response.
When switching a patient from immediate-release capsules to Lithium Carbonate Extended-Release Tablets, give the same total daily dose when possible. Most patients on maintenance therapy are stabilized on 900 mg daily, e.g., Lithium Carbonate Extended-Release Tablets 450 mg b.i.d. When the previous dosage of immediate-release lithium is not a multiple of 450 mg, e.g., 1,500 mg, initiate Lithium Carbonate Extended-Release Tablets at the multiple of 450 mg nearest to, but below, the original daily dose, i.e., 1,350 mg. When the 2 doses are unequal, give the larger dose in the evening. In the above example, with a total daily dose of 1,350 mg, generally 450 mg of Lithium Carbonate Extended-Release Tablets should be given in the morning and 900 mg of Lithium Carbonate Extended-Release Tablets in the evening. If desired, the total daily dose of 1,350 mg can be given in 3 equal 450-mg doses of Lithium Carbonate Extended-Release Tablets. These patients should be monitored at 1- to 2-week intervals, and dosage adjusted if necessary, until stable and satisfactory serum levels and clinical state are achieved.
When patients require closer titration than that available with doses of Lithium Carbonate Extended-Release Tablets in increments of 450 mg, immediate-release capsules should be used.
Acute Mania: Optimal patient response to Lithium Carbonate Extended-Release Tablets can usually be established and maintained with 1,800 mg per day in divided doses. Such doses will normally produce the desired serum lithium level ranging between 1.0 and 1.5 mEq/L.

Dosage must be individualized according to serum levels and clinical response. Regular monitoring of the patient’s clinical state and serum lithium levels is necessary. Serum levels should be determined twice per week during the acute phase, and until the serum level and clinical condition of the patient have been stabilized.
Long-Term Control:The desirable serum lithium levels are 0.6 to 1.2 mEq/L. Dosage will vary from one individual to another, but usually 900 mg to 1,200 mg per day in divided doses will maintain this level. Serum lithium levels in uncomplicated cases receiving maintenance therapy during remission should be monitored at least every two months.
Patients unusually sensitive to lithium may exhibit toxic signs at serum levels below 1.0 mEq/L.

Important Considerations

• Blood samples for serum lithium determinations should be drawn immediately prior to the next dose when lithium concentrations are relatively stable (i.e., 8 to 12 hours after the previous dose). Total reliance must not be placed on serum levels alone. Accurate patient evaluation requires both clinical and laboratory analysis.

• Elderly patients often respond to reduced dosage, and may exhibit signs of toxicity at serum levels ordinarily tolerated by younger patients.

• Lithium Carbonate Extended-Release Tablets must be swallowed whole and never chewed or crushed.

HOW SUPPLIED

Lithium Carbonate Extended-Release Tablets 450 mg are supplied as white to off white round tablets scored on one side and engraved with P; 450 on the other side.

NDC: 70518-2086-00

PACKAGING: 30 in 1 BLISTER PACK

Storage Condition: Store at 25°C (77°F), excursions permitted to 15-30°C (59-86°F) [see USP Controlled Room Temperature].

Repackaged and Distributed By:

Remedy Repack, Inc.

625 Kolter Dr. Suite #4 Indiana, PA 1-724-465-8762

PACKAGE LABEL

DRUG: Lithium Carbonate

GENERIC: Lithium Carbonate

DOSAGE: TABLET, EXTENDED RELEASE

ADMINSTRATION: ORAL

NDC: 70518-2086-0

COLOR: white

SHAPE: ROUND

SCORE: Two even pieces

SIZE: 11 mm

IMPRINT: P;450

PACKAGING: 30 in 1 BLISTER PACK

ACTIVE INGREDIENT(S):

- LITHIUM CARBONATE 450mg in 1

INACTIVE INGREDIENT(S):

- SODIUM ALGINATE
- SODIUM STARCH GLYCOLATE TYPE A POTATO
- FERRIC OXIDE YELLOW
- MAGNESIUM STEARATE
- POVIDONE K30